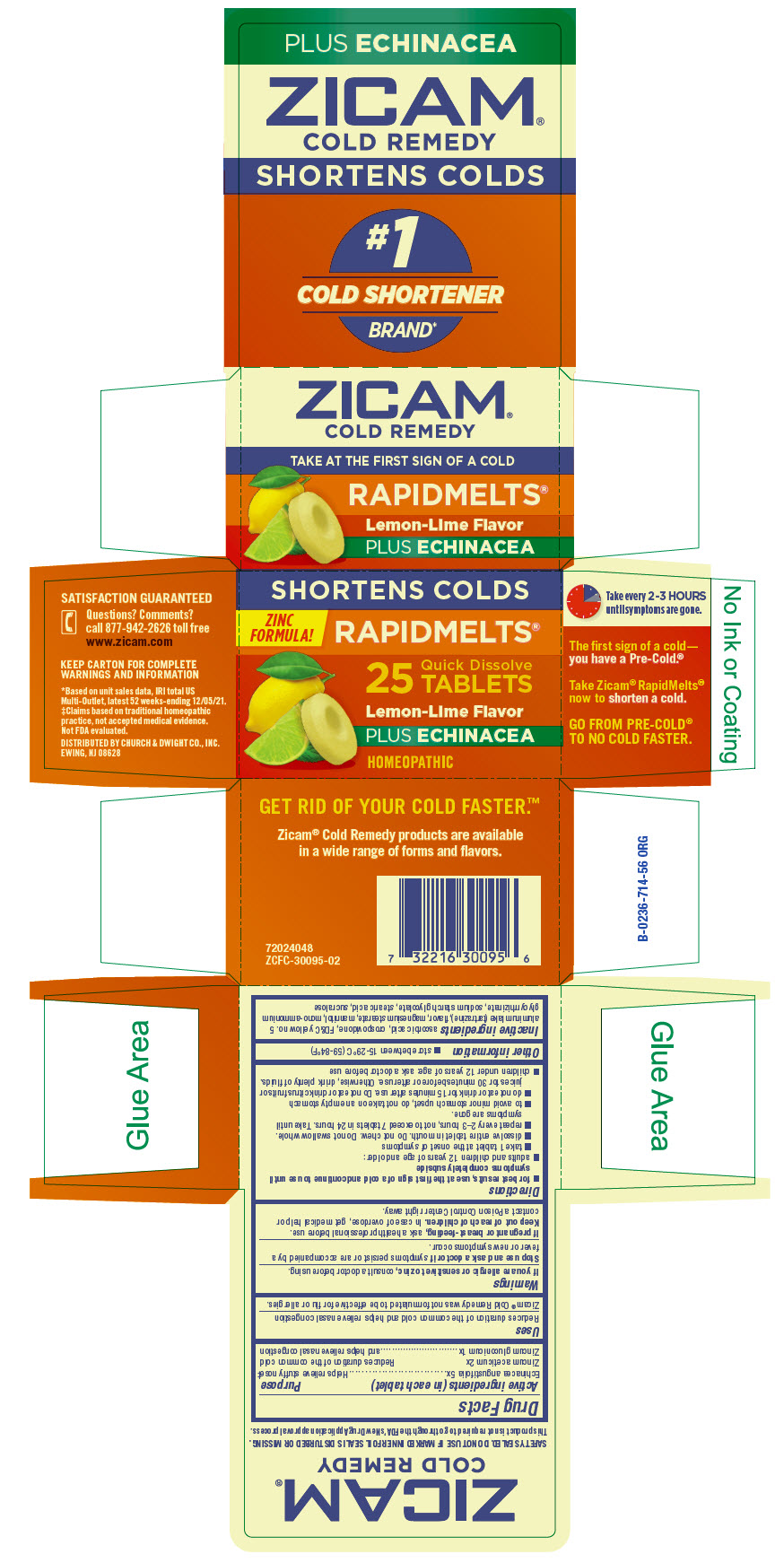 DRUG LABEL: Zicam 
NDC: 10237-477 | Form: TABLET
Manufacturer: CHURCH & DWIGHT CO., INC.
Category: homeopathic | Type: HUMAN OTC DRUG LABEL
Date: 20230124

ACTIVE INGREDIENTS: ZINC ACETATE ANHYDROUS 2 [hp_X]/1 1; ECHINACEA ANGUSTIFOLIA WHOLE 5 [hp_X]/1 1; ZINC GLUCONATE 1 [hp_X]/1 1
INACTIVE INGREDIENTS: ascorbic acid; CROSPOVIDONE (120 .MU.M); FD&C Yellow No. 5; aluminum oxide; magnesium stearate; mannitol; ammonium glycyrrhizate; stearic acid; sucralose; sodium starch glycolate type a potato

Zicam®
Cold Remedy Rapidmelts with Echinacea

Drug Facts

ACTIVE INGREDIENT

Active ingredients (in each tablet) | Purpose
Echinacea angustifolia 5x | Helps relieve stuffy nose [Claims based on traditional homeopathic practice, not accepted medical evidence. Not FDA evaluated.]
Zincum aceticum 2x Zincum gluconicum 1x | Reduces duration of the common cold and helps relieve nasal congestion

Uses

Reduces duration of the common cold and helps relieve nasal congestion

Zicam® Cold Remedy was not formulated to be effective for flu or allergies.

Warnings

ASK DOCTOR

If you are allergic or sensitive to zinc, consult a doctor before using.

Stop use and ask a doctor if symptoms persist or are accompanied by a fever or new symptoms occur.

PREGNANCY OR BREAST FEEDING

If pregnant or breast-feeding, ask a health professional before use.

Keep out of reach of children. In case of overdose, get medical help or contact a Poison Control Center right away.

Directions

- for best results, use at the first sign of a cold and continue to use until symptoms completely subside
- adults and children 12 years of age and older:
  - take 1 tablet at the onset of symptoms
  - dissolve entire tablet in mouth. Do not chew. Do not swallow whole.
  - repeat every 2 – 3 hours, not to exceed 7 tablets in 24 hours. Take until symptoms are gone.
  - to avoid minor stomach upset, do not take on an empty stomach
  - do not eat or drink for 15 minutes after use. Do not eat or drink citrus fruits or juices for 30 minutes before or after use. Otherwise, drink plenty of fluids.
- children under 12 years of age: ask a doctor before use

Other information

- store between 15-29°C (59-84°F)

Inactive ingredients

ascorbic acid, crospovidone, FD&C yellow no. 5 aluminum lake (tartrazine), flavor, magnesium stearate, mannitol, mono-ammonium glycyrrhizinate, sodium starch glycolate, stearic acid, sucralose

Questions? Comments?

call 877-942-2626 toll free

DISTRIBUTED BY CHURCH & DWIGHT CO., INC.
EWING, NJ 08628

PRINCIPAL DISPLAY PANEL - 25 Tablet Bottle Carton

SHORTENS COLDS

ZINC
FORMULA!

RAPIDMELTS®

25
Quick Dissolve
TABLETS

Lemon-Lime Flavor

PLUS ECHINACEA

HOMEOPATHIC